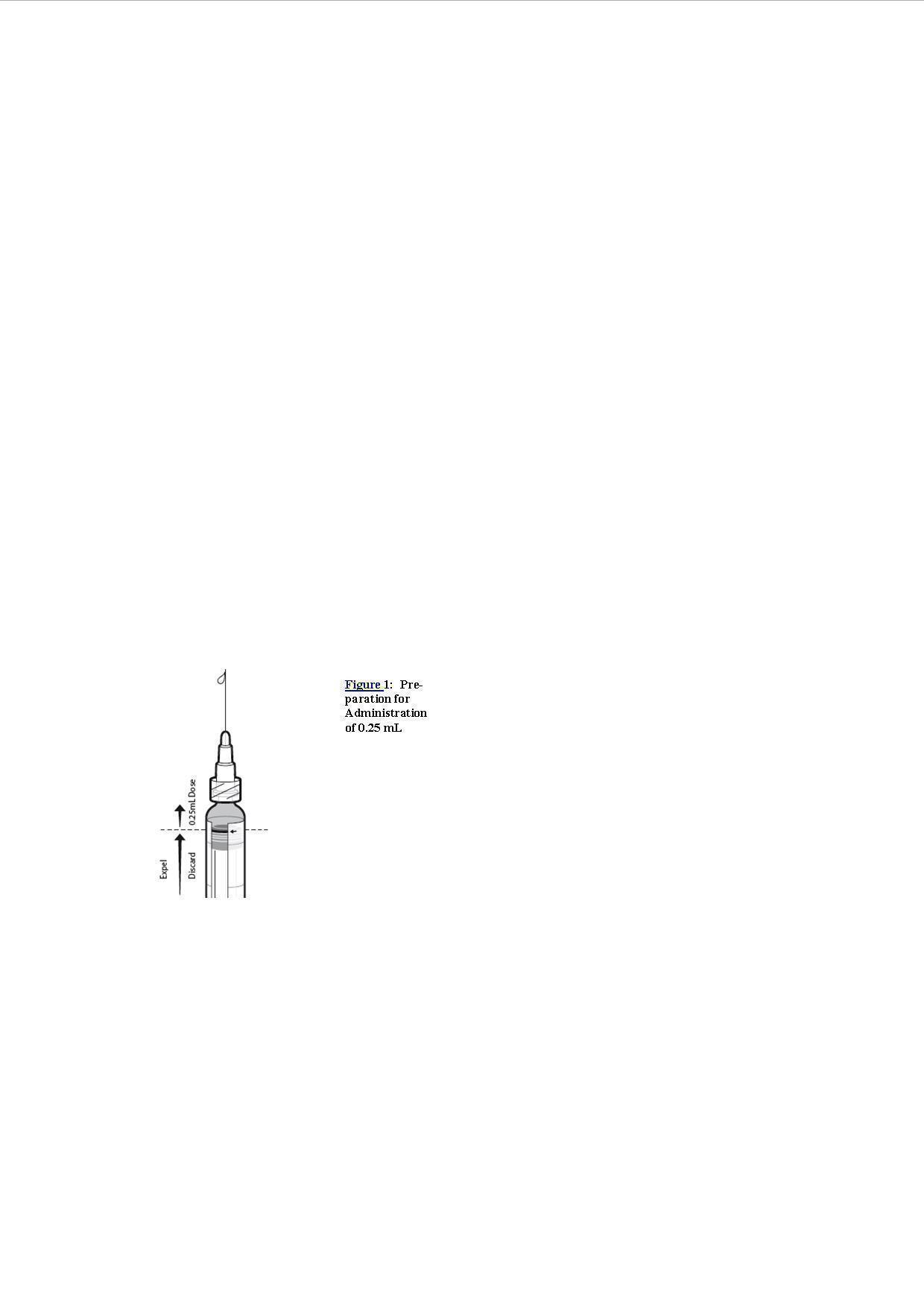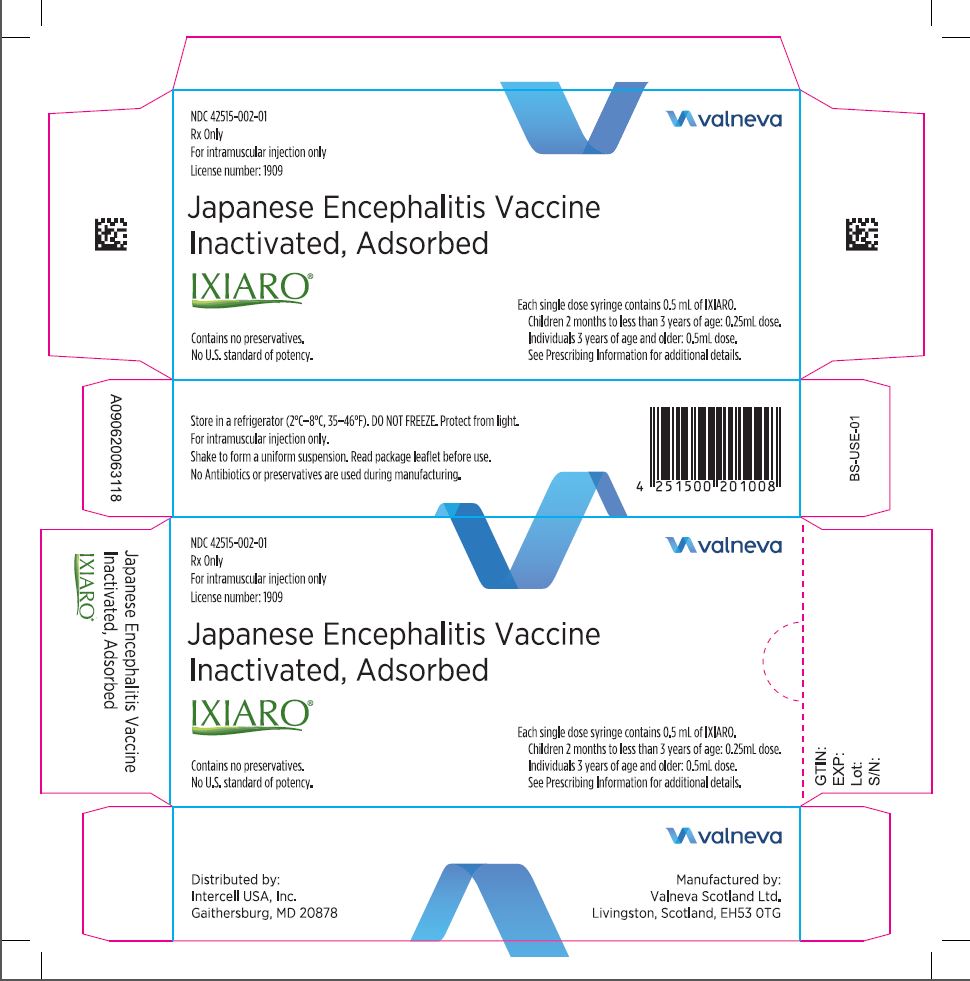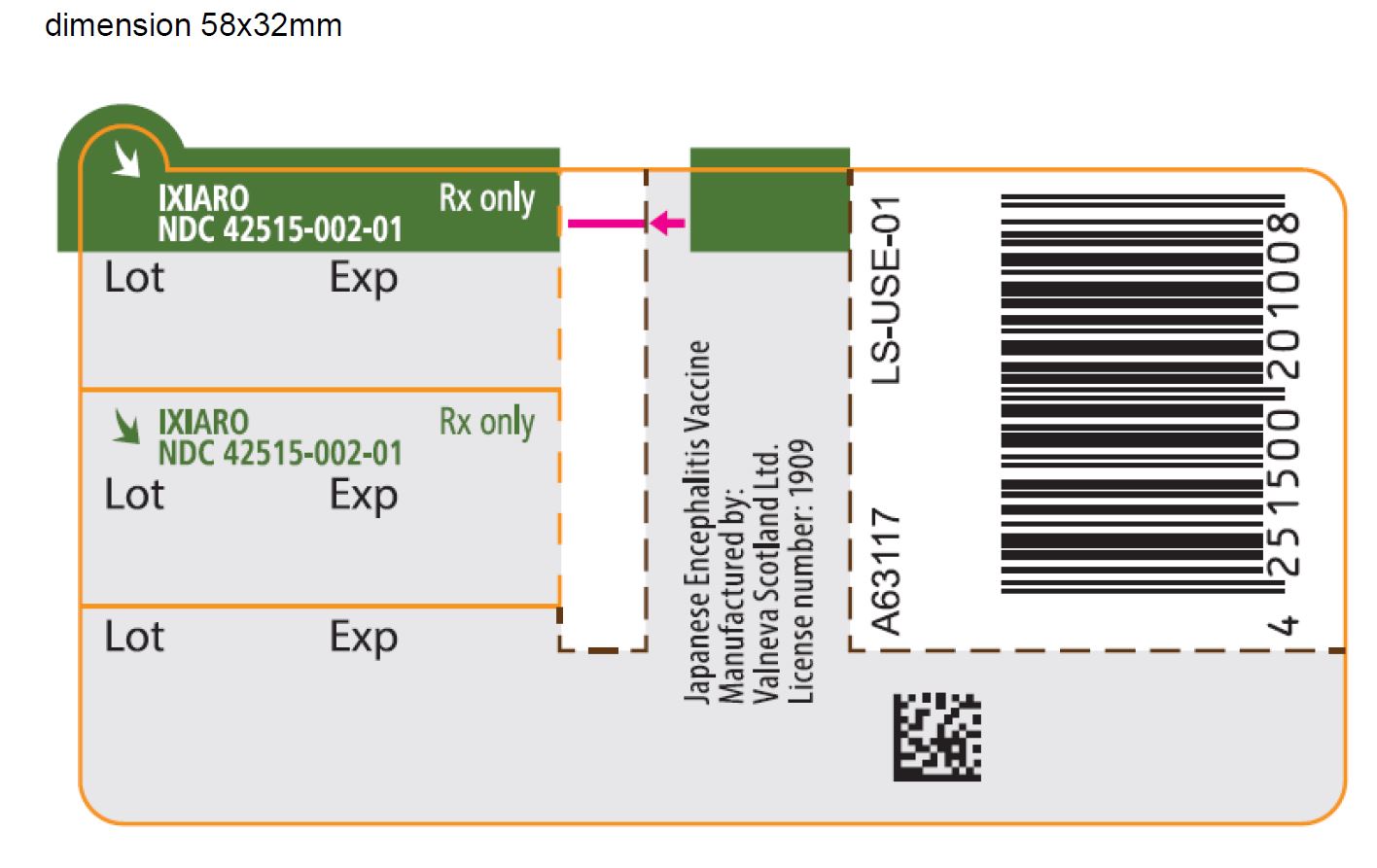 DRUG LABEL: IXIARO
NDC: 42515-002 | Form: INJECTION, SUSPENSION
Manufacturer: Valneva Scotland Ltd.
Category: other | Type: VACCINE LABEL
Date: 20221205

ACTIVE INGREDIENTS: JAPANESE ENCEPHALITIS VIRUS STRAIN SA 14-14-2 ANTIGEN (FORMALDEHYDE INACTIVATED) 6 [arb'U]/0.5 mL
INACTIVE INGREDIENTS: ALUMINUM HYDROXIDE 250 ug/0.5 mL

HIGHLIGHTS OF PRESCRIBING INFORMATION

These highlights do not include all the information needed to use IXIARO safely and effectively. See full prescribing information for IXIARO.
IXIARO (Japanese Encephalitis Vaccine, Inactivated, Adsorbed)
Suspension for Intramuscular Injection
Initial U.S. Approval: 2009

1 INDICATIONS AND USAGE

- IXIARO is a vaccine indicated for active immunization for the prevention of disease caused by Japanese encephalitis virus (JEV). IXIARO is approved for use in individuals 2 months of age and older. (1)

2 DOSAGE AND ADMINISTRATION

For intramuscular administration only.

Age | Dose* | Primary Series
Children 2 months to <3 years of age | 0.25 mL | 2 doses, 28 days apart
Individuals 3 years of age and older | 0.5 mL | 2 doses, 28 days apart

*To administer a 0.25 mL dose, expel and discard half of the volume from the 0.5 mL pre-filled syringe by pushing the plunger stopper up to the edge of the red line on the syringe barrel prior to injection. (2.3)

Complete the primary immunization series at least 1 week prior to potential exposure to JEV. (2.1, 14)

Individuals 17 years of age and older who have received a primary immunization series more than 1 year previously may be given a booster dose if ongoing exposure or re-exposure to JEV is expected. (2.1)

3 DOSAGE FORMS AND STRENGTHS

- Suspension for injection supplied in 0.5 mL single dose syringes.

4 CONTRAINDICATIONS

Severe allergic reaction, (e.g., anaphylaxis,) after a previous dose of IXIARO, any other Japanese Encephalitis Virus vaccine, or any component of IXIARO, including protamine sulfate, is a contraindication to administration of IXIARO. (4)

5 WARNINGS AND PRECAUTIONS

IXIARO contains protamine sulfate, a compound known to cause hypersensitivity reactions in some individuals. (5.1)

6 ADVERSE REACTIONS

In infants 2 months to <1 year of age, the most common injection site reaction was redness (>15%); the most common solicited systemic adverse reactions were fever (>20%), irritability (>15%) and diarrhea (>10%). (6.1)
In children 1 to <3 years of age, the most common solicited systemic adverse reaction was fever (>20%). (6.1)
In children 3 to <12 years of age, the most common solicited systemic adverse reaction was fever (>10%). (6.1)
In adolescents 12 to <18 years of age, the most common injection site reactions were pain (15%) and tenderness (10%). (6.1)
In adults 18 years of age and older, the most common injection site reactions were pain (>25%) and tenderness (>25%); the most common solicited systemic adverse reactions were headache (>20%) and myalgia (>10%). (6.1)

To report SUSPECTED ADVERSE REACTIONS, contact Intercell USA Inc. at 844-349-4276 (8443-IXIARO) or VAERS at 1 800 822 7967 or www.vaers.hhs.gov.

8 USE IN SPECIFIC POPULATIONS

To report inadvertent use in pregnant women, contact Intercell USA Inc. at 1-844-349-4276 (8443-IXIARO).

See 17 for PATIENT COUNSELING INFORMATION and FDA‑approved patient labeling (Patient Information).

Revised 03/2017

FULL PRESCRIBING INFORMATION

1 INDICATIONS AND USAGE

IXIARO is a vaccine indicated for the prevention of disease caused by Japanese encephalitis virus (JEV). IXIARO is approved for use in individuals 2 months of age and older.

2 DOSAGE AND ADMINISTRATION

For intramuscular administration only.

2.1 Dosage and Schedule

Primary Series:
Children 2 months to <3 years of age: Primary immunization with IXIARO consists of two (2) 0.25 mL doses, administered 28 days apart.
Individuals 3 years of age and older: Primary immunization with IXIARO consists of two (2) 0.5 mL doses, administered 28 days apart.
Complete the primary immunization series at least 1 week prior to potential exposure to JEV.

Booster Dose:
Individuals 17 years of age and older: If the primary series of two doses was completed more than 1 year previously, a booster dose may be given if ongoing exposure or re-exposure to JEV is expected.
Infants, children and adolescents 2 months to <17 years of age: The safety and immunogenicity of a booster dose has not been evaluated.

2.2 Administration

IXIARO is administered intramuscularly. The preferred sites for intramuscular injection are the anterolateral aspect of the thigh in infants 2 to 11 months of age, the anterolateral aspect of the thigh (or the deltoid muscle if muscle mass is adequate) in children 1 to <3 years of age, or the deltoid muscle in individuals 3 years of age and older.
Do not administer intravenously, intradermally, or subcutaneously.

2.3 Preparation for Administration

Prior to agitation, IXIARO is a clear liquid with a white precipitate. Before administration, shake the syringe well to obtain a white, opaque, homogeneous suspension.
Parenteral drug products should be inspected visually for particulate matter and discoloration prior to administration. If either of these conditions exists, do not administer.
Preparation of a 0.25 mL Dose of IXIARO for Administration to Children 2 Months to <3 Years of Age:
1. Shake the pre-filled syringe containing 0.5 mL to obtain a homogeneous suspension.
2. Remove the syringe tip cap by gently twisting it. Do not attempt to snap or pull the tip off as this may damage the syringe.
3. Attach a sterile safety needle to the pre-filled syringe (needle is not provided with IXIARO).
4. Hold the syringe in an upright position and uncap the needle.
5. Push the plunger stopper up to the edge of the red line on the syringe barrel, indicated by a red arrow (see Figure1)*, and discard expelled volume into a medical waste container.
6. Lock the needle safety shield and remove the needle.
7. Attach a new sterile needle prior to injection of the remaining volume.
*If the plunger stopper is pushed beyond the red line, do not administer the vaccine. Repeat the procedure using a new pre-filled syringe.
Preparation of a 0.5 mL Dose of IXIARO for Administration to Individuals 3 Years of Age and Above:
1. Shake the pre-filled syringe containing 0.5 mL to obtain a homogeneous suspension.
2. Remove the syringe tip cap by gently twisting it. Do not attempt to snap or pull the tip off as this may damage the syringe.
3. Attach a sterile needle to the pre-filled syringe (needle is not provided with IXIARO).

3 DOSAGE FORMS AND STRENGTHS

IXIARO is a suspension for injection supplied in 0.5 mL single dose syringes. For children 2 months to <3 years of age, a single dose is 0.25 mL. For individuals 3 years of age and older, a single dose is 0.5 mL. [See Dosage and Administration (2.1)]

4 CONTRAINDICATIONS

Severe allergic reaction (e.g., anaphylaxis) after a previous dose of IXIARO, any other Japanese Encephalitis Virus vaccine, or any component of IXIARO, including protamine sulfate, is a contraindication to administration of IXIARO [See Description (11)]. Alternatively, because of uncertainty as to which component of the vaccine may be responsible, individuals with a history of severe allergic reaction to another Japanese Encephalitis vaccine may be referred to an allergist for evaluation if immunization with IXIARO is considered.

5 WARNINGS AND PRECAUTIONS

5.1 Hypersensitivity Reactions

IXIARO contains protamine sulfate, a compound known to cause hypersensitivity reactions in some individuals [See Description (11)].

Appropriate medical care should be readily available in case of anaphylactic reaction.

5.2 Limitations of Vaccine Effectiveness

Vaccination with IXIARO may not protect all individuals.

5.3 Altered Immunocompetence

Immunocompromised individuals may have a diminished immune response to IXIARO.

6 ADVERSE REACTIONS

In infants 2 months to <1 year of age, the most common injection site reaction was redness (>15%); the most common solicited systemic adverse reactions were fever (>20%), irritability (>15%) and diarrhea (>10%). In children 1 to <3 years of age, the most common solicited systemic adverse reaction was fever (>20%). In children 3 to <12 years of age, the most common solicited systemic adverse reaction was fever (>10%). In adolescents 12 to <18 years of age, the most common solicited injection site reactions were pain (15%) and tenderness (10%). In adults 18 years of age and older, the most common injection site reactions were pain (>25%) and tenderness (>25%); the most common solicited systemic adverse reactions were headache (>20%) and myalgia (>10%).

6.1 Clinical Trials Experience

Because clinical trials are conducted under widely varying conditions, adverse reaction rates observed in the clinical trials of a vaccine cannot be directly compared to rates in the clinical trials of another vaccine and may not reflect the rates observed in practice.

Clinical Studies in Children 2 Months to <18 Years of Age:

Adverse Events in a Pediatric Trial Comparing IXIARO to U.S.-Licensed Control Vaccines HAVRIX and PREVNAR:

The safety of IXIARO was evaluated in a randomized, controlled, open-label clinical trial in healthy male and female subjects 2 months to <18 years of age, conducted in the Philippines, a country where Japanese Encephalitis is endemic (Study 1)^1. IXIARO was compared to two control vaccines: HAVRIX (Hepatitis A vaccine, pediatric 720 EL.U./0.5 mL formulation, GlaxoSmithKline Biologicals) and Prevnar (Pneumococcal 7-valent Conjugate Vaccine [Diphtheria CRM197 protein], Pfizer). A total of 1,769 subjects were randomized in an age-stratified scheme in a 3:1 ratio (2:1 ratio for ages <1 year) to receive intramuscular injections of either IXIARO (two 0.25 mL doses on Days 0 and 28 for infants and children 2 months to <3 years of age or two 0.5 mL doses on Days 0 and 28 for children 3 to <18 years of age) or HAVRIX (children 1 year of age and older, 2 doses on Day 0 and at Month 7) or Prevnar (infants 2 to <6 months of age, 3 doses on Days 0, 28, 56 and an optional 4th dose at Month 7 or later; infants 6 to <12 months of age, 3 doses on Days 0 and 56 and at Month 7). Subject numbers and dosing schemes by age group are displayed in Table 1.

Table 1. Subject Numbers and Dosing Schemes by Age Group (Safety Population, Study 1§,Philippines)

Treatment Group | IXIARO*; (N=1311) | HAVRIX; (N=394) | PREVNAR; (N=64)
Subjects in Age Group 2 months to <1 year | 131 | - | 64
Subjects in Age Group 1 year to <3 years | 640 | 213 | -
Subjects in Age Group 3 to <12 years | 300 | 101 | -
Subjects in Age Group 12 to <18 years | 240 | 80 | -

§ NCT01041573

*Infants and children 2 months to <3 years of age received two 0.25 mL doses administered on Days 0 and 28. Individuals 3 years of age and older received two 0.5 mL doses administered on Days 0 and 28.

Analysis of safety in children was carried out using the safety population including 1,311 subjects receiving at least one dose of IXIARO, 394 subjects receiving the first dose of HAVRIX on Day 0, and 64 subjects receiving at least one dose of Prevnar on Day 0 (all infants <1 year of age). The IXIARO and control groups were similar with regard to demographics (mean age 5.48 years, range 2 months to 17 years; 49.5% female; ethnicity: Asian: 100% for Study 1 overall). Parents or subjects recorded adverse events on a diary card for the first seven days after each vaccination. Only those events considered to be assessable based on the subjects developmental status were recorded. Parents or subjects were queried regarding the occurrence of any unsolicited AEs following the previous vaccination at in-person visits, which included a medical exam, on Day 28, Day 56, and at Month 7.

Solicited Adverse Events

For an overview of solicited local and systemic reactions for pediatric age groups see Table 2 (infants 2 months to <1 year of age), Table 3 (toddlers 1 to <3 years of age) Table 4 (children 3 to <12 years of age), and Table 5 (adolescents 12 to <18 years of age). As children 1 year of age and older received the second dose of HAVRIX at the final study visit at Month 7, rates of solicited AEs among these subjects after the second vaccination are only available for IXIARO.

Table 2.Rates of Solicited Adverse Reactions on Days 0-7 After Each Vaccination in Infants 2 Months to <1 Year of Age, by Dose and Treatment Group, Study 1§,Philippines

 | Post Dose 1; (% of subjects) | Post Dose 2; (% of subjects)
Injection Site Reactions | IXIARO*; (N=131‡) | Prevnar; (N=64‡) | IXIARO*; (N=131‡) | Prevnar; (N=64‡)
Tenderness | 3.1 | 12.7 | 0.8 | 3.3
Hardening | 0.0 | 7.9 | 0.0 | 1.6
Swelling | 1.5 | 6.3 | 1.5 | 1.6
Redness | 17.6 | 25.4 | 5.3 | 16.4
Solicited Systemic Reactions
Irritability | 15.3 | 12.7 | 8.4 | 8.2
Vomiting | 7.6 | 6.3 | 3.8 | 1.6
Diarrhea | 11.5 | 6.3 | 8.4 | 4.9
Excessive fatigue | 3.1 | 7.9 | 1.5 | 3.3
Rash | 8.4 | 9.5 | 3.8 | 4.9
Loss of appetite | 5.3 | 9.5 | 5.3 | 6.6
Fever ≥37.7°C (≥99.9°F) | 23.7 | 25.4 | 14.5 | 23.3
37.7-38.6 °C (99.9-101.5°F) | 17.6 | 22.2 | 12.2 | 15.0
38.7-39.3 °C (101.6-102.7°F) | 6.1 | 1.6 | 1.5 | 6.7
39.4-40.5 °C (102.8-104.9°F) | 0.0 | 1.6 | 0.8 | 1.7
>40.5°C (>104.9°F) | 0.0 | 0.0 | 0.0 | 0.0

§ NCT01041573

*IXIARO dose 0.25 mL.

‡N=number of subjects with available diary card data after each dose, used as the denominator to calculate percentages.

Table 3. Rates of Solicited Adverse Reactions on Days 0-7 After Each Vaccination in Children 1 Year to <3 Years of Age, by Dose and Treatment Group, Study 1§,Philippines

 | Post Dose 1; (% of subjects**) |  | Post Dose 2; (% of subjects**)
Injection Site Reactions | IXIARO*; (N=640‡) |  | Havrix; (N=213‡) | IXIARO*; (N=637‡)
Pain | 3.6 (6/165) |  | 7.4 (4/54) | 3.6 (6/166)
Itching | 0.6 (1/180) |  | 0.0 (0/63) | 0.0 (0/184)
Tenderness | 3.1 |  | 5.6 | 1.4
Hardening | 0.9 |  | 0.5 | 0.3
Swelling | 2.0 |  | 3.3 | 1.7
Redness | 6.1 |  | 7.5 | 2.5
Solicited Systemic Reactions
Irritability | 7.7 |  | 5.6 | 2.7
Nausea | 2.2 (5/228) |  | 1.3 (1/78) | 0.9 (2/229)
Vomiting | 4.2 |  | 5.6 | 2.8
Diarrhea | 7.0 |  | 5.2 | 4.6
Flu-like symptoms | 7.7 (13/169) |  | 13.3 (8/60) | 4.0 (7/176)
Excessive fatigue | 2.5 |  | 0.9 | 1.1
Muscle pain | 2.3 (3/130) |  | 0.0 (0/42) | 0.7 (1/136)
Rash | 4.2 |  | 2.3 | 1.3
Headache | 1.5 (2/135) |  | 4.4 (2/45) | 1.4 (2/143)
Loss of appetite | 5.6 |  | 4.2 | 2.5
Fever ≥37.7°C (≥99.9°F) | 20.2 |  | 15.5 | 12.7
37.7-38.6 °C (99.9-101.5°F) | 15.6 |  | 12.2 | 8.5
38.7-39.3 °C (101.6-102.7°F) | 3.0 |  | 1.4 | 2.5
39.4-40.5 °C (102.8-104.9°F) | 1.6 |  | 1.9 | 1.6
>40.5°C (>104.9°F) | 0.0 |  | 0.0 | 0.2

§NCT01041573
*IXIARO dose 0.25 mL.
‡N=number of subjects with available diary card data after each dose, used as the denominator to calculate percentages
** Where the number of subjects with available data for a particular symptom differed from the overall number of subjects with available diary card data, the rate (n/N) is provided; n is the number of subjects who reported that symptom, and N is the number of subjects with available data for that symptom.

Table 4. Rates of Solicited Adverse Reactions on Days 0-7 After Each Vaccination in Children 3 Years to <12 Years of Age, by Dose and Treatment Group, Study 1§,Philippines

 | Post Dose 1; (% of subjects) | Post Dose 2; (% of subjects)
Injection Site Reactions | IXIARO*; (N=291-300‡) | Havrix; (N=99-101‡) | IXIARO*; (N=293-300‡)
Pain | 5.5 | 3.0 | 1.7
Itching | 1.4 | 0.0 | 0.0
Tenderness | 4.3 | 1.0 | 2.0
Hardening | 1.3 | 0.0 | 0.0
Swelling | 2.0 | 3.0 | 2.0
Redness | 3.0 | 1.0 | 0.7
Solicited Systemic Reaction
Irritability | 0.0 | 1.0 | 0.3
Nausea | 0.3 | 0.0 | 0.3
Vomiting | 1.7 | 1.0 | 0.7
Diarrhea | 0.7 | 0.0 | 1.0
Flu-like symptoms | 1.4 | 2.0 | 0.3
Excessive fatigue | 1.0 | 1.0 | 0.7
Muscle pain | 2.4 | 3.0 | 0.3
Rash | 1.0 | 0.0 | 0.0
Headache | 3.8 | 4.0 | 1.4
Loss of appetite | 1.0 | 2.0 | 1.0
Fever ≥37.7°C (≥99.9°F) | 10.7 | 8.9 | 4.7
37.7-38.6 °C (99.9-101.5°F) | 7.7 | 6.9 | 3.3
38.7-39.3 °C (101.6-102.7°F) | 2.0 | 2.0 | 0.7
39.4-40.5 °C (102.8-104.9°F) | 1.0 | 0.0 | 0.7
>40.5°C (>104.9°F) | 0.0 | 0.0 | 0.0

§NCT01041573
*IXIARO dose 0.5 mL.
‡N=range of subjects with available diary card data after each dose, used as denominators to calculate percentages.

Table 5. Rates of Solicited Adverse Reactions on Days 0-7 After Each Vaccination in Children 12 Years to <18 Years of Age, by Dose and Treatment Group, Study 1§, Philippines

 | Post Dose 1; (% of subjects) | Post Dose 2; (% of subjects)
Injection Site Reactions | IXIARO*; (N=240‡) | Havrix; (N=80‡) | IXIARO*; (N=238‡)
Pain | 15.0 | 12.5 | 6.7
Itching | 0.8 | 0.0 | 0.4
Tenderness | 10.0 | 13.8 | 4.6
Hardening | 1.3 | 0.0 | 0.4
Swelling | 0.4 | 1.3 | 0.8
Redness | 0.8 | 6.3 | 3.8
Solicited Systemic Reaction
Irritability | 2.1 | 1.3 | 0.0
Nausea | 2.1 | 1.3 | 0.0
Vomiting | 1.3 | 0.0 | 0.0
Diarrhea | 0.4 | 2.5 | 0.0
Flu-like symptoms | 3.3 | 7.5 | 1.3
Excessive fatigue | 2.5 | 1.3 | 0.4
Muscle pain | 2.9 | 5.0 | 1.3
Rash | 0.8 | 1.3 | 0.0
Headache | 4.6 | 5.0 | 3.4
Loss of appetite | 2.1 | 2.5 | 0.4
Fever ≥37.7°C (≥99.9°F) | 3.8 | 6.3 | 5.0
37.7-38.6 °C (99.9-101.5°F) | 3.3 | 3.8 | 3.8
38.7-39.3 °C (101.6-102.7°F) | 0.4 | 1.3 | 1.3
39.4-40.5 °C (102.8-104.9°F) | 0.0 | 1.3 | 0.0
>40.5°C (>104.9°F) | 0.0 | 0.0 | 0.0

§NCT01041573
*IXIARO dose 0.5 mL.
‡N=number of subjects with available diary card data after each dose, used as the denominator to calculate percentages.

Serious Adverse Events

There was one death due to disseminated intravascular coagulation following suspected bacterial meningitis in a 12 year old male 4 months after the second dose of IXIARO. Forty serious adverse events (SAEs) were reported during the 7 month study period. Twenty-three subjects (1.6%) who received IXIARO, 1 subject (1.6%) who received Prevnar and 10 subjects (2.5%) who received HAVRIX experienced an SAE. Some subjects experienced more than one SAE.

The SAEs occurring most frequently in all study groups were febrile convulsions. A total of 12 febrile convulsions were reported (9 of them as SAEs), in 8 subjects (1.0% of children below the age of 3 years) receiving IXIARO, 3 subjects (1.4% of children below the age of 3 years) receiving HAVRIX and 1 subject (1.6%) receiving Prevnar. All febrile convulsions occurred in children below the age of 3 years. Onset of febrile convulsions ranged from 2 days to >5 months after doses of IXIARO with no apparent temporal clustering, 4 weeks after Prevnar and 9 days to >16 weeks after HAVRIX.

Adverse Events in a Pediatric Trial^2 of IXIARO in Children Traveling from Western Countries:

The safety of IXIARO was evaluated in an ongoing, uncontrolled, open-label clinical trial conducted in the United States, Europe and Australiain healthy children with planned travel to JEV-endemic areas (Study 2)^2. IXIARO (0.25 mL dose for children 2 months to <3 years of age, 0.5 mL dose for children and adolescents 3 to <18 years of age) was administered by intramuscular injection on Day 0 and Day 28. An analysis of safety was carried out after enrolment of 60 subjects (mean age: 12.50 years, range 10 months to 17 years; 56.7% female; ethnicity: White: 83.3%, Asian: 13.3%, Black: 3.3%). Parents or subjects recorded adverse events on a diary card for the first seven days after each vaccination. Only those events considered to be assessable based on the subjects developmental status were recorded. Parents or subjects were queried about the occurrence of unsolicited AEs through 6 months after the last vaccination (Month 7).

At the time of the analysis, 40% (2/5) subjects 2 months to <3 years of age experienced injection site hardening, injection site redness, and diarrhea following the first or second dose of IXIARO. Solicited adverse reactions among subjects 3 to <18 years of age are summarized in Table 6.

Table 6. Rates of Solicited Adverse Reactions on Days 0-7 After Each IXIARO 0.5 mL Vaccination in Children 3 Years to <18 Years of Age Traveling From Western Countries, Study 2§

 | Post Dose 1; (N=55); % of subjects | Post Dose 2; (N=49); % of subjects
Injection Site Reactions
Pain | 18.2 | 16.3
Itching | 3.6 | 2.0
Tenderness | 30.9 | 24.5
Hardening | 0.0 | 2.0
Swelling | 0.0 | 0.0
Redness | 5.5 | 0.0
Solicited Systemic Reaction
Irritability | 0.0 | 6.1
Nausea | 1.8 | 2.0
Vomiting | 0.0 | 2.0
Diarrhea | 1.8 | 0.0
Flu-like symptoms | 0.0 | 0.0
Excessive fatigue | 12.7 | 0.0
Muscle pain | 27.3 | 2.0
Rash | 1.8 | 2.0
Headache | 1.8 | 4.1
Loss of appetite | 1.8 | 0.0
Fever 37.7°C (99.9°F) | 5.5 | 2.0
37.7-38.6 °C (99.9-101.5°F) | 3.6 | 2.0
38.7-39.3 °C (101.6-102.7°F) | 1.8 | 0.0
39.4-40.5 °C (102.8-104.9°F) | 0.0 | 0.0
>40.5°C (>104.9°F) | 0.0 | 0.0

§NCT01047839
‡N=number of subjects with available diary card data after each dose, used as the denominator to calculate percentages.

Clinical Studies in Adults 18 Years of Age and Older:

In five randomized, controlled clinical studies^3, 4, 5, 6, 7 conducted in North America, Europe, Australia and New Zealand, a total of 3,558 healthy adults 18 to 86 years of age received at least one dose of IXIARO and were followed-up for safety for 6 months after the first dose. In this pooled dataset of subjects who received IXIARO, one death occurred in a subject with metastatic lung adenocarcinoma four months after completing the two-dose regimen. About 1% of subjects who received IXIARO experienced a serious adverse event, including one case of multiple sclerosis. Approximately 1% of subjects who received IXIARO discontinued due to adverse events.

Adverse Events in a Clinical Trial Comparing IXIARO to a Control in Adults:

The safety of IXIARO was evaluated in a randomized, controlled, double‑blind clinical trial in healthy male and female subjects 18 years of age (Study 3)^3. IXIARO was compared to a control: Phosphate Buffered Saline containing 0.1% aluminum hydroxide [PBS + Al(OH)3]. A total of 2,675 subjects were randomized in a 3:1 ratio to receive either an intramuscular injection of IXIARO (0.5 mL) each on Day 0 and Day 28, or an intramuscular injection of PBS + Al(OH)3 (0.5 mL) each on Day 0 and Day 28. Analysis of safety was carried out using the safety population including 1,993 subjects receiving at least one dose of IXIARO and 657 subjects receiving at least one dose of PBS + Al(OH)3 (mean age: 33.8 years, range 18 to 86 years; 55.3% female; ethnicity: White: 91.7%, Asian: 1.8%, Black: 3.4%, Other: 3.0%). The IXIARO and control groups were similar with regard to demographics. Subjects recorded adverse events on a diary card for the first seven days after each vaccination. In addition, the study investigator took a medical history and performed a physical exam to evaluate for adverse events on the day of each vaccination and at a visit 4 weeks after the second vaccination.

Serious Adverse Events

No deaths occurred during this trial. Sixteen serious adverse events (SAE) were reported during the study period. Ten subjects (0.5%) who received IXIARO and 6 subjects (0.9%) who received PBS + Al(OH)3 experienced a SAE. The serious adverse events occurring in the IXIARO group were as follows: Dermatomyositis, appendicitis, rectal hemorrhage, limb abscess (contralateral to the injected arm), chest pain, ovarian torsion, ruptured corpus luteal cyst, and three orthopedic injuries.

Systemic Adverse Events

Overall, the percentage of subjects who experienced at least one adverse event during the study period was 58.9% in the IXIARO group compared to 56.6% in the PBS + Al(OH)3 group. Adverse events of any severity grade occurring with an incidence of 1% of subjects are shown in Table 7. Most adverse events (>90%) were mild to moderate.

Table 7. Rates of Common Solicited and Unsolicited Systemic Adverse Events* in Adults Residing in Non-Endemic Areas After IXIARO or Control [PBS + Al(OH)3], Safety Population, Study 3§

 | Post Dose 1 (Day 0 to Day 28); % of subjects | Post Dose 2 (Day 28 to Day 56); % of subjects | Post Dose 1 or Dose 2 (Day 0 to Day 56); % of subjects
Adverse Event | IXIARO N‡=1993 | PBS + Al(OH)3 N‡=657 | IXIARO N‡=1968 | PBS + Al(OH)3 N‡=645 | IXIARO N‡=1993 | PBS + Al(OH)3 N‡=657
Headache† | 21.6 | 20.2 | 13.4 | 13.0 | 27.9 | 26.2
Myalgia† | 13.3 | 12.9 | 5.6 | 5.3 | 15.6 | 15.5
Fatigue† | 8.6 | 8.7 | 5.2 | 5.9 | 11.3 | 11.7
Influenza-like Illness† | 8.2 | 8.5 | 5.8 | 4.3 | 12.3 | 11.7
Nausea† | 4.7 | 5.3 | 2.6 | 3.7 | 6.6 | 7.5
Nasopharyngitis | 2.3 | 1.8 | 2.6 | 2.3 | 4.7 | 4.0
Fever† | 1.9 | 2.1 | 1.5 | 1.7 | 3.2 | 3.0
Rhinitis | 1.0 | 0.8 | 0.5 | 0.6 | 1.4 | 1.4
Upper Respiratory Tract Infection | 0.9 | 0.9 | 0.8 | 0.9 | 1.7 | 2.0
Back Pain | 0.8 | 0.9 | 0.6 | 0.2 | 1.3 | 1.1
Pharyngolaryngeal Pain | 0.8 | 0.9 | 1.0 | 0.5 | 1.6 | 1.4
Rash† | 0.8 | 0.9 | 0.7 | 0.8 | 1.3 | 1.5
Diarrhea | 0.8 | 0.8 | 0.7 | 0.3 | 1.5 | 1.1
Cough | 0.8 | 0.8 | 0.6 | 0.6 | 1.2 | 1.2
Vomiting† | 0.6 | 0.8 | 0.8 | 0.9 | 1.4 | 1.7

§NCT00605085
*The adverse events in this table are those observed at an incidence of ≥1% in the IXIARO or PBS + Al(OH)3 groups.
† These symptoms were solicited in a subject diary card. Percentages also include unsolicited events that occurred after the 7 day period covered by the diary card.
‡N=number of subjects in the safety population (subjects treated with at least one dose) who received the respective dose

Injection Site Reactions

Injection site reactions after IXIARO were compared to reactions after PBS + Al(OH)3. Symptoms were recorded into a subject diary for the first seven days after each injection, and the injection site was assessed by the investigator at each visit. The rates of injection site reactions are shown in Table 8. Most injection site reactions (>90%) were mild to moderate.

Table 8. Rates of Injection Site Solicited Adverse Reactions* After IXIARO or Control [PBS + Al(OH)3], Adults Residing in Non-Endemic Areas, Safety Population With Evaluable Diary Cards, Study 3§

 | Post Dose 1; (% of subjects†) | Post Dose 2; (% of subjects†) | Post Dose 1 or Dose 2; (% of subjects†)
Adverse Reaction | IXIARO N‡=1963 | PBS + Al(OH)3 N‡=645 | IXIARO N‡=1951 | PBS + Al(OH)3 N‡=638 | IXIARO N‡=1963 | PBS + Al(OH)3 N‡=645
Any Reaction | 48.5 | 47.7 | 32.6 | 32.2 | 55.4 | 56.2
Pain | 27.7 | 28.2 | 17.7 | 18.2 | 33.0 | 35.8
Tenderness | 28.8 | 26.9 | 22.5 | 18.1 | 35.9 | 32.6
Erythema | 6.8 | 5.4 | 4.6 | 4.1 | 9.6 | 7.4
Induration | 4.8 | 5.3 | 4.0 | 3.0 | 7.5 | 7.4
Edema | 2.4 | 3.3 | 2.3 | 1.6 | 4.2 | 4.6
Pruritus | 2.6 | 3.3 | 1.6 | 1.9 | 3.8 | 4.5

§NCT00605085
* Injection site reactions were assessed for 7 days after each dose.
† Denominators used to calculate percentages are based on the number of evaluable diary card entries (defined as documented presence on any day [i.e., entry of “yes”] or absence on all days [i.e., entry of “no”]) for each individual symptom and observation period.
‡N=number of subjects who returned diary cards after each dose

Adverse Events in a Clinical Trial Comparing IXIARO to JE-VAX in Adults:

The safety of IXIARO compared to another U.S.-licensed inactivated JE vaccine (JE-VAX) was evaluated in a randomized, double-blind clinical trial in subjects 18 years of age (Study 4)^4.

No deaths occurred during this trial. One serious adverse event occurred in this trial in a subject with a history of myocardial infarction (MI) who experienced a MI three weeks after receiving the 2nd dose of IXIARO. The most common adverse events after immunization occurring in 1% of subjects were headache, myalgia, fatigue, influenza-like illness, nausea, nasopharyngitis, fever, pharyngolaryngeal pain, cough, rash, diarrhea, sinusitis, upper respiratory tract infection, back pain, migraine, vomiting and influenza, which occurred with similar frequency in both treatment groups. Local injection site reactions solicited in diary cards for 7 days after each vaccination were observed at a rate of 54% in the IXIARO group (N=428) compared to a rate of 69.1% in the JE-VAX group (N=435).

Adverse Events in a Clinical Trial Investigating a Booster Dose of IXIARO in Adults:

The safety of a booster dose of IXIARO administered 14 months after completion of the primary series was evaluated in an open-label, uncontrolled study in subjects 18 years of age (Study 8)^8.

Within 28 days of booster vaccination, adverse events were reported by 35.4% of subjects (N=198). Within 12 months of booster vaccination, subjects who experienced at least one adverse event were 56.1%. Injection site reactions were reported in the subject diary for 30.8% of subjects within 7 days of booster vaccination. Adverse events considered by the investigators to be treatment-related were recorded for 11.6% of subjects (these related events were all observed within one month after the booster dose administration).

The most common injection site reactions (>10% of subjects) were pain (12.8%) and tenderness (19.2%); the most common systemic adverse events (>10%) were nasopharyngitis (15.2%) and headache (11.1%).

Safety in Concomitant Use with the Hepatitis A Vaccine, HAVRIX in Adults (Study 6)^6

The safety of IXIARO when administered concomitantly with inactivated Hepatitis A Virus vaccine (HAVRIX) was evaluated in a controlled trial in which subjects 18 years of age were assigned randomly to one of three treatment groups: Group A (N=62) received IXIARO + HAVRIX; Group B (N=65) received IXIARO + control [PBS + Al(OH)3]; Group C (N=65) received HAVRIX + control [PBS + Al(OH)3]. One serious adverse event occurred in this trial in a subject with a history of alcoholism and seizure disorder who experienced a seizure three weeks after receiving the 2nd dose of IXIARO + control.

The percentage of subjects who experienced at least one adverse event was as follows: Group A: 38.7%; Group B: 41.5%; Group C: 47.7%. The most frequently reported injection site reaction on the day of the first vaccination in all three groups was injection site pain in 59.0% of subjects in Group A, in 48.4% of subjects in Group B and in 48.4% of subjects in Group C.

6.2 Post-Marketing Experience

The following additional adverse reactions have been identified during post approval use of IXIARO. Because these reactions are reported voluntarily from a population of uncertain size, it is not always possible to estimate reliably their frequency or establish a causal relationship to the vaccine.
Nervous system disorders: Paraesthesia, Neuritis.

7 DRUG INTERACTIONS

7.1 Use with HAVRIX

In one clinical trial^6 in adults, IXIARO was administered concomitantly with HAVRIX (Hepatitis A Vaccine) [See Adverse Reactions (6) and Clinical Studies (14)]. In this trial, there was no evidence for interference with the immune response to IXIARO or to HAVRIX when HAVRIX was administered concomitantly with dose 1 of IXIARO [See Clinical Studies (14)]. Data are not available on concomitant administration of IXIARO with other US-licensed vaccines.

When IXIARO is administered concomitantly with injectable vaccines, they should be given with separate syringes at different injection sites. IXIARO should not be mixed with any other vaccine in the same syringe or vial.

7.2 Use with Immunosuppressive Therapies

Immunosuppressive therapies may decrease the immune response to IXIARO [See Warnings and Precautions (5)].

8 USE IN SPECIFIC POPULATIONS

8.1 Pregnancy

Pregnancy category B. Reproduction studies have been performed in female rats at doses approximately 300-fold excess relative to the projected human dose (on a mg/kg basis) and have revealed no evidence of impaired fertility or harm to the fetus due to IXIARO. There are, however, no adequate and well‑controlled studies in pregnant women. Because animal reproduction studies are not always predictive of human response, IXIARO should be used during pregnancy only if clearly needed.

The effect of IXIARO vaccine on embryo-fetal and pre-weaning development was evaluated in a developmental toxicity study using pregnant rats. One group of rats was administered IXIARO twice prior to gestation and once during the period of organogenesis (gestation Day 6). A second group of pregnant rats was administered IXIARO once prior to gestation and once during the period of organogenesis (gestation Day 6). IXIARO was administered at 0.5 mL/rat/occasion (approximately 300-fold excess relative to the projected human dose on a mg/kg basis), by intramuscular injection. No adverse effects on mating, fertility, pregnancy, parturition, lactation, embryo-fetal or pre-weaning development were observed. There was a statistically significant finding of incomplete ossification in a few fetuses derived from the second group of pregnant rats. However, there are no data to suggest that this finding is vaccine related. There were no vaccine-related fetal malformations or other evidence of teratogenesis noted in this study.

Healthcare practitioners are encouraged to report inadvertent use in pregnant women to the distributor, Intercell USA Inc., at 1-844-349-4276 (8443-IXIARO).

8.3 Nursing Mothers

It is not known whether this vaccine is excreted in human milk. Because many drugs are excreted in human milk, caution should be exercised if IXIARO is administered to a nursing woman.

8.4 Pediatric Use

Safety and effectiveness of IXIARO have not been established in infants younger than 2 months of age [See Adverse Reactions (6) and Clinical Studies (14)].

8.5 Geriatric Use

Clinical studies of IXIARO did not include sufficient numbers of subjects 65 years of age and older to determine whether they respond differently from younger subjects. In a study that included 24 subjects ≥65 years of age who received IXIARO per protocol (Study 6)^6, the proportion of these subjects achieving a JEV neutralizing antibody titer ≥1:10 at 28 days after the second dose of IXIARO was 95.8% (geometric mean titer: 255.2).

In subjects 65 years of age and older who had been vaccinated in any of five trials^3 ,^4 ,^5 ,^6 ,^7 included in a pooled dataset (N=161), adverse events were reported in 61.9% (73/118) of subjects in the IXIARO group, 57.7% (15/26) in the JE-VAX group, and 70.6% (12/17) in the control [PBS + Al(OH)3] group. Serious adverse events (SAE) were experienced by four subjects (3.4%) who received IXIARO, no subjects who received JE-VAX, and one subject (5.9%) who received the control [PBS + Al(OH)3]. The SAEs occurring in the IXIARO group were as follows: one case each of rectal hemorrhage, pancreatic adenocarcinoma, breast cancer, and one death in a subject with metastatic lung adenocarcinoma, which occurred four months after the subject completed the two-dose regimen.

11 DESCRIPTION

IXIARO, Japanese Encephalitis Vaccine, Inactivated, Adsorbed is a sterile suspension for intramuscular injection. Each 0.5 mL dose of vaccine contains 6 antigen units of purified, inactivated JEV and approximately 250 mcg of aluminum hydroxide. The appearance of the liquid is a white, opaque, non-uniform suspension which becomes homogeneous upon shaking.
IXIARO is a vaccine prepared by propagating JEV strain SA14-14-2 in Vero cells. Multiple viral harvests are pooled, clarified and concentrated. The virus suspension is treated with protamine sulfate to remove contaminating DNA and proteins. The resulting partially purified virus is processed through a sucrose density gradient centrifugation step and fractionated. Each fraction is analyzed for the presence of virus, and fractions with the highest virus activity are pooled to give a purified virus suspension. The purified virus is then inactivated by treatment with formaldehyde. The preparation is adjusted to a specified antigen content and formulated by addition of aluminum hydroxide.
The formulated bulk vaccine is filled into syringes, at a volume of 0.5 mL per syringe. From the manufacturing process, IXIARO also contains: formaldehyde (not more than 200 ppm), bovine serum albumin (not more than 100 ng/mL), host cell DNA (not more than 200 pg/mL), sodium metabisulphite (not more than 200 ppm), host cell protein (not more than 100 ng/mL), and protamine sulfate (not more than 1µg/mL). No preservatives, stabilizers, or antibiotics are added to the formulation.

12 CLINICAL PHARMACOLOGY

12.1 Mechanism of Action

Japanese encephalitis is a disease caused by the mosquito-borne Japanese encephalitis virus (JEV). IXIARO acts by inducing antibodies that neutralize live JEV. Accumulated data from animal studies, clinical trials of other JE vaccines, and human epidemiological studies, suggest that a virus neutralizing antibody response, as measured in vitro in a 50% plaque-reduction neutralization antibody test (PRNT50) with a threshold titer of ≥1:10, provides evidence of protective immunity^(10, 11). The evaluation of vaccine effectiveness of IXIARO was therefore based on neutralizing antibody response using a threshold PRNT50 titer of ≥1:10.

13 NONCLINICAL TOXICOLOGY

13.1 Carcinogenesis, Mutagenesis, Impairment of Fertility

IXIARO has not been evaluated for carcinogenic or mutagenic potential. IXIARO was found to have no effect on fertility of female rats at intramuscular doses of up to 300‑fold excess relative to the projected human dose (on a mg/kg basis) administered prior to and after mating [See Use in Specific Populations (8.1)]. The effect of IXIARO on male fertility has not been evaluated.

14 CLINICAL STUDIES

Immunogenicity of IXIARO in a Pediatric Clinical Trial in the Philippines

The immunogenicity of IXIARO was evaluated in a subgroup of children included in a randomized, controlled, open-label clinical trial in healthy children conducted in the Philippines (Study 1)^1in which the safety of IXIARO was compared to control vaccines: HAVRIX (Hepatitis A vaccine, pediatric 720 EL.U./0.5 mL formulation) and Prevnar (Pneumococcal 7-valent Conjugate Vaccine [Diphtheria CRM197 protein]). Subjects in the IXIARO treatment arm received intramuscular doses on Day 0 and Day 28. A total of 396 subjects from the group receiving an age-appropriate dosage of IXIARO (0.25 mL for infants and children 2 months to <3 years of age or 0.5 mL for individuals 3 to <18 years of age) were randomized in an age-stratified scheme into the immunogenicity subgroup (mean age: 7.7 years; 49.6% female; ethnicity: 100% Asian). [ See Adverse Reactions (6.1)]

The immunogenicity evaluation included the proportion of subjects with PRNT50 titer ≥1:10 and geometric mean titer (GMT) at Day 56 and Month 7. The JEV-neutralizing antibody responses elicited by IXIARO in the Intent-to-Treat population (defined as all subjects who received at least one dose of IXIARO) are presented in Table 9.

Table 9. JEV-Neutralizing Antibody Response After IXIARO* Among Children 2 Months to <18 Years of Age Residing in the Philippines, Intent-To-Treat Population**, Study 1§

Age Group | 2 months – <6 months | 6 months – <12 months | 1 year – <3 years | 3 years - <12 years | 12 years - <18 years
Time Point | Proportion of Subjects with PRNT50 Titer ≥1:10 (n/N) [95% CI]
Pre-Vaccination Screen | 30% (3/10) [10.8, 60.3] | 0% (0/20); [0.0, 16.1] | 3.2% (4/125); [1.3, 7.9] | 16.8% (17/101) [10.8, 25.3] | 45.7% (64/140) [37.7, 54.0]
Day 56; (28 days after vaccine dose 2) | 100% (9/9); [70.1, 100.0] | 100% (19/19); [83.2, 100.0] | 99.2% (119/120); [95.4, 99.9] | 100.0% (100/100); [96.3, 100.0] | 100% (137/137) [97.3, 100.0]
Month 7; (6 months after vaccine dose 2) | 100% (10/10); [72.2, 100.0] | 100% (18/18); [82.4, 100.0] | 85.5% (106/124); [78.2, 90.6] | 91.0% (91/100); [83.8, 95.2] | 97.1% (133/137); [92.7, 98.9]
Time Point | Geometric Mean Titers◊ (N) [95% CI]
Pre-Vaccination Screen | 8.4; (10); [4.3, 16.7] | 5.0; (20); [5.0, 5.0] | 5.5; (124); [ 5.0, 6.1] | 6.5; (101); [ 5.8, 7.4] | 13.1; (140); [ 10.7, 16.1]
Day 56; (28 days after vaccine dose 2) | 687.4; (9) [263.2, 1795.1] | 377.8; (19) [210.3, 678.8] | 258.9; (121); [214.4, 312.6] | 213.7; (100); [175.6, 260.0] | 175.6; (137); [147.8, 208.7]
Month 7; (6 months after vaccine dose 2) | 159.3; (10) [110.0, 230.7] | 64.0; (18) [39.4, 104.1] | 38.9; (125); [31.8, 47.7] | 43.6; (100); [35.6, 53.4] | 86.6; (137) [70.7, 106.0]

§ 01041573

*Infants and children ≥2 months to <3 years of age received two 0.25 mL doses administered on Days 0 and 28. Individuals 3 years of age and older received two 0.5 mL doses administered on Days 0 and 28.

**The Intent to Treat population consisted of all subjects who received at least one dose of IXIARO.

N=number of subjects with data available

n=number of subjects with a PRNT50 titer ≥1:10

◊Reciprocal titers <10 were imputed to 5.

Immunogenicity of IXIARO in a Pediatric Clinical Study in Children 2 Months to <18 Years of Age Traveling from Non-Endemic Countries

The immunogenicity of IXIARO was evaluated in an uncontrolled, open-label clinical study conducted in the United States, Europe and Australia in healthy male and female children with planned travel to JEV-endemic areas (Study 2)^2. IXIARO (0.25 mL dose for children 2 months to <3 years of age, 0.5 mL dose for children and adolescents 3 to <18 years of age) was administered by intramuscular injection on Day 0 and Day 28. An analysis was carried out on immunogenicity data for the first 54 subjects enrolled (median age: 15.2 years, range 10 months to 17 years; 59.3% female; ethnicity: White: 81.5%, Asian: 14.8%, Black: 3.7%). [ See Adverse Reactions (6.1)]

JEV neutralizing antibody titers were available for 51 subjects at Day 56 (5 subjects 2 months to <3 years of age and 46 subjects 3 to <18 years of age) and for 18 subjects at Month 7 (2 subjects 2 months to <3 years of age and 16 subjects 3 to <18 years of age). All subjects had PRNT50 titers ≥1:10 at Day 56 and Month 7, and GMTs were similar to those among children vaccinated with IXIARO in a study conducted in the Philippines, where JEV is endemic (see Table 9).

Immunogenicity of IXIARO in a Clinical Trial in Adults

Immunogenicity of the vaccine was evaluated in a randomized, active‑controlled, observer‑blinded clinical trial conducted in the U.S., Germany and Austria (Study 4)^4 in 867 healthy adults 18 years of age and older (mean age: 41.3 years; 60.8% female; ethnicity: White 80.8%, Asian 0.8%, Black 13.1%, Other 5.3%). Subjects in the IXIARO treatment arm received the following schedule of three intramuscular doses: Day 0, IXIARO, Day 7, PBS + Al(OH)3 (0.5 mL phosphate buffered saline with 0.1% aluminum hydroxide), and on Day 28, IXIARO. Subjects in the comparator arm received a subcutaneous dose of 1.0 mL of the US‑licensed JEV vaccine, JE-VAX, on Days 0, 7 and 28. [ See Adverse Reactions (6.1)]

The proportion of subjects with, PRNT50 titer ≥1:10, and GMT were evaluated at Day 56 in the per protocol population which included all subjects who had no major protocol deviations and who had a PRNT50 titer <1:10 at baseline. The neutralizing antibody responses elicited by IXIARO met predefined statistical criteria for non-inferiority compared to those induced by JE‑VAX, and are presented in Table 10. All subjects were seronegative at baseline (PRNT50 titer <1:10).

Table 10. JEV-Neutralizing Antibody Response After IXIARO or JE‑VAX Among Adults Residing in Non-Endemic Areas, Per Protocol Population*, Study 4§

Proportion of Subjects with PRNT50 Titer ≥1:10
Time Point | IXIARO(n/N); [95% CI] | JE‑VAX (n/N); [95% CI] | Rate difference; [95% CI]
Day 56; (28 days after vaccine dose 2) | 96.4% (352/365); [94.0, 97.9] | 93.8% (347/370); [90.9, 95.8] | 2.6%; [-0.5,6.0]†
Geometric Mean Titers◊
Time Point | IXIARO (N**=361); [95% CI] | JE‑VAX (N**=364); [95% CI] | GMT ratio; [95% CI]
Day 56; (28 days after vaccine dose 2) | 243.6 [ 216.4, 274.1] | 102.0 [90.3, 115.2 ] | 2.33 [1.97, 2.75]‡

§ 00604708

*The Per Protocol population consisted of subjects with no major protocol deviations and a PRNT50 titer <1:10 at baseline

† Non-inferiority was demonstrated if the lower bound of the 2-sided 95% confidence interval (CI) for the difference in proportion of subjects with PRNT50 titer ≥1:10 (IXIARO minus JE‑VAX) was >‑10% at Day 56.
‡ Non-inferiority was demonstrated if the lower bound of the 2-sided 95% CI for the GMT ratio (IXIARO /JE‑VAX) was >1/1.5 at Day 56.
n=number of subjects with a PRNT50 titer ≥1:10
N=number of subjects in the Per Protocol Population
**N=Number of subjects with immunogenicity data
◊Reciprocal titers <10 were imputed to 5.

Temporal Evaluation of Immunogenicity of IXIARO During Vaccination Series in Adults

In a randomized, observer-blinded clinical study in 374 healthy adults 18 years of age and older (Study 5)^5, the immunogenicity of IXIARO was evaluated on days 10, 28, 35, and 56 during the vaccination period. The proportion of subjects with PRNT50 titer ≥1:10 at each time point for the subjects randomized to the standard dosing regimen (IXIARO on days 0 and 28) are displayed in Table 11.

Table 11. JEV-Neutralizing Antibody Response During the Vaccination Series (IXIARO on Days 0 and 28) Among Adults Residing in Non-Endemic Areas, Per Protocol Population*, Study 5§

Time Point | Proportion of Subjects with PRNT50 Titer ≥1:10 (n/N) [95% CI]
Day 10 (10 days after vaccine dose 1) | 21.1% (24/114); [13.6%; 28.5%]
Day 28; (28 days after vaccine dose 1) | 39.8% (45/113); [30.8%; 48.8%]
Day 35 (7 days after vaccine dose 2) | 97.3% (110/113); [94.4%; 100.0%]
Day 56; (28 days after vaccine dose 2) | 97.3% (110/113); [94.4%, 100%]

§ 00505790

*The Per Protocol population consisted of all subjects with no major protocol deviations
n=number of subjects with a PRNT50 titer ≥1:10

N=number of subjects with immunogenicity data

Persistence of Neutralizing Antibody Response in Adults

The persistence of JEV-neutralizing antibody was evaluated in a subgroup of adult subjects recruited for follow-up after participation in one of two clinical trials (Study 4 and Study 5)^(4, 5). In the Intent-to-Treat population of subjects randomized to vaccination with IXIARO (N=181) and in the population of subjects who intended to stay in the study until month 36 (ITT36, N = 152), the proportion of subjects with PRNT50 titer ≥1:10 at 6, 12, 24 and 36 months after initiation of the two-dose series were 95% [95% CI 90.8, 97.4], 83.4% [95% CI 77.3, 88.1] , 81.8% [95% CI 75.5, 86.7] and 84.9% [95% CI 78.3, 89.7], respectively. Geometric mean titers (GMT) at 6, 12, 24 and 36 months after initiation of the two-dose series were 83.5 [95% CI 70.9, 98.4], 41.2 [95% CI 34.4, 49.3], 44.3; [95% CI 36.7, 53.4] and 43.8 [95% CI 36.5, 52.6], respectively.

In another study with 116 adults who completed the IXIARO primary immunization series (Study 9)^9, the proportions of subjects with PRNT50 titers ≥1:10 at 11 and 23 months after completion of the primary series were 58.3% [95% CI 49.1, 66.9] and 48.3% [95% CI 39.4, 57.3], respectively, and GMTs were 18.0 [95% CI 14.3, 22.6] and 16.2 [95% CI 12.6, 20.8].

Immunogenicity of IXIARO Booster Doses in Adults

A single booster dose of IXIARO was evaluated in 198 adult subjects enrolled in an uncontrolled, open-label phase 3 study. IXIARO was administered 14 months after completion of the primary series (Study 8)^8. The JEV neutralizing antibody responses from this study are presented in Table 12.

Table 12. JEV-Neutralizing Antibody Response Following a Booster Dose of IXIARO Administered 14 Months After Completion of the Primary Series Among Adults Residing in Non-Endemic Areas, Intent to Treat Population*, Study 8§

Time Point | % PRNT Titer ≥1:10 (n/N); [95% CI] | Geometric Mean Titers (N) [95% CI]
Pre-booster, Day 0 | 69.2% (137/198) [62.4%, 75.2%] | 22.5 (198) [19.0, 26.7]
Day 28 | 100.0% (198/198) [98.1%, 100.0%] | 900.1 (198) [742.4, 1091.3]
Month 6 | 98.5% (194/197) [95.6%, 99.5%] | 487.4 (197) [390.7, 608.1]
Month 12 | 98.5% (191/194) [95.6%, 99.5%] | 361.4 (194) [294.5, 443.5]

§ 00595309

*The Intent to Treat population consisted of all subjects who received the booster vaccination

n=number of subjects with a PRNT50 titer ≥1:10

N=number of subjects with immunogenicity data

The immunogenicity of booster doses was assessed in adult subjectsin another study investigating persistence of immunity following vaccination with the primary series of IXIARO (Study 5)^5. Subjects with PRNT50 titers <1:10 at 11 months after completion of the primary series received a booster dose of IXIARO 11 months later (22 months after completion of the primary series). Among 27 subjects with available immunogenicity data at 4 weeks after the booster dose, the proportion of subjects with PRNT50 titer ≥1:10 was 100% [95% CI 87.5, 100.0], and the GMT was 2536.7 [95% CI 1467.7, 4384.4].

Concomitant Administration of IXIARO and Hepatitis A Vaccine, HAVRIX in Adults

The concomitant use of IXIARO with inactivated Hepatitis A Virus vaccine (HAVRIX) was evaluated in a randomized, controlled, single‑blind clinical trial including 192 healthy adults 18 to 61 years of age (Study 7)^7. Subjects were divided into three treatment groups: Group A (N=62) received IXIARO (Day 0 and 28) + HAVRIX (Day 0); Group B (N=65) received IXIARO (Day 0 and 28) + control (0.5 mL phosphate buffered saline with 0.1% aluminum hydroxide by intramuscular injection on Day 0); Group C (N=65) received HAVRIX (Day 0) + control (Day 0 and 28). Anti-JEV GMT at Day 56 in Group A met non-inferiority criteria compared to anti-JEV GMT at Day 56 in Group B. In addition, anti-HAV GMT at Day 28 in Group A met non-inferiority criteria compared to anti-HAV GMT at Day 28 in Group C. Therefore, concomitant administration of IXIARO and HAVRIX did not adversely affect immunogenicity compared to administration of either vaccine individually. Safety results regarding co-administration of IXIARO with HAVRIX are summarized in Adverse Reactions (6.1).

Delayed Completion of Primary Immunization in Adults

The immunogenicity of a second dose of the primary series administered 11 months after dose 1 was assessed in 100 adults in a study investigating persistence of immunity following vaccination with different dose-schedules of IXIARO (Study 5)^5. Four weeks after this delayed second dose, 99.0% of subjects (99/100) had a PRNT50 titer ≥1:10 (GMT 504.3 [95% CI: 367.3, 692.3]). One year later, 88.5% of subjects (85/96) had a PRNT50 titer ≥1:10 (GMT 121.0 [95% CI: 87.4, 167.6]).

15 REFERENCES

1. Clinical study referred to as NCT01041573 in the National Library of Medicine clinical trial database, also referred to as study IC51-323 in the Biologics License Application
2. Clinical study referred to as NCT01047839 in the National Library of Medicine clinical trial database, also referred to as study IC51-322 in the Biologics License Application
3. Clinical study referred to as NCT00605085 in the National Library of Medicine clinical trial database, also referred to as study IC51-302 in the Biologics License Application
4. Clinical study referred to as NCT00604708 in the National Library of Medicine clinical trial database, also referred to as study IC51-301 in the Biologics License Application.
5. Clinical study referred to as NCT00595790 in the National Library of Medicine clinical trial database, also referred to as study IC51-304 in the Biologics License Application.
6. Clinical study referred to as NCT00596271 in the National Library of Medicine clinical trial database, also referred to as study IC51-308 in the Biologics License Application.
7. Clinical study referred to as NCT00594958 in the National Library of Medicine clinical trial database, also referred to as study IC51-309 in the Biologics License Application.
8. Clinical study referred to as NCT00595309 in the National Library of Medicine clinical trial database, also referred to as study IC51-311 in the Biologics License Application.
9. Clinical study referred to as NCT00595270 in the National Library of Medicine clinical trial database, also referred to as study IC51-305 in the Biologics License Application.
10. Hoke CH, Nisalak A, Sangawhipa N, Jatanasen S, Laorakapongse T, Innis BL, Kotchasenee S, Gingrich JB, Latendresse J, Fukai K, et al. Protection against Japanese encephalitis by inactivated vaccines. N Engl J Med. 1988 Sep 8;319(10):608-14.
11. Hombach J, Solomon T, Kurane I, Jacobson J, Wood D. Report on a WHO consultation on immunological endpoints for evaluation of new Japanese encephalitis vaccines, WHO, Geneva, 2-3 September, 2004. Vaccine. 2005;23:5205-11.

16 HOW SUPPLIED/STORAGE AND HANDLING

16.1 How Supplied

IXIARO is supplied as a sterile 0.5 mL suspension in a pre filled syringe (Type I glass) with a plunger stopper (chlorobutyl elastomer) in a pack size of 1 single-dose syringe with or without a separate needle. See Section 2.3 for information on preparing a 0.25 mL dose for children 2 months to <3 years of age and a 0.5 mL dose for individuals 3 years of age and older. NDC 42515-002-01.

Neither the syringe nor the packaging materials are made with natural rubber latex.

16.2 Storage and Handling

Store in a refrigerator at 2° to 8° C (35° to 46° F). Do not freeze.

Do not use the vaccine after the expiration date shown on the label. Store in the original package in order to protect from light. During storage, a clear liquid with a white precipitate can be observed.

17 PATIENT COUNSELING INFORMATION

Question the vaccine recipient about reactions to previous vaccines, and inform the vaccine recipient of the benefits and risks of IXIARO.
Consult current U.S. and international advisories regarding prevalence of Japanese encephalitis in specific locations. Advise the parent, guardian, or recipient that IXIARO may not fully protect everyone who gets the vaccine and that personal precautions should be taken to reduce exposure to mosquito bites (adequate clothing, use of repellents, mosquito nets).
Give the parent, guardian, or recipient the Vaccine Information Statements, which are required by the National Childhood Vaccine Injury Act of 1986 to be given prior to immunization, and inquire about previous reactions to vaccines.

Inform the parent, guardian, or recipient of the importance of completing the immunization series.

Instruct the parent, guardian, or recipient to immediately report any signs and/or symptoms of a severe adverse reaction, including anaphylaxis (difficulty breathing, wheezing, weakness or fast heart beat, hives).

Manufactured by:
Valneva Scotland Ltd.
Oakbank Park Road, EH53 0TG, Livingston, UK
T: +44.1506.446.600
F: +44.1506.446.601
www.valneva.com

Distributed by:
Valneva USA, Inc.
Bethesda, MD 20814
USA

Patient Information about

IXIARO (pronounced “ĭk-sē-ah-rō”)

Generic name: Japanese encephalitis vaccine, inactivated, adsorbed

Read this information about IXIARO before you are vaccinated. If you have any questions about IXIARO after reading this leaflet, ask your health care provider. This leaflet does not take the place of talking with your health care professional about IXIARO. Only your health care provider can decide if IXIARO is right for you.

What is IXIARO and how does it work?

- IXIARO is a vaccine for use in individuals 2 months of age and older to help protect against Japanese encephalitis (JE). You cannot get the disease from IXIARO.
- You will need 2 doses of the vaccine.
- You should consult your health care provider on the need for a booster dose of IXIARO
- You should still protect yourself from mosquito bites even if you have had the IXIARO vaccine.
- IXIARO may not fully protect everyone who gets the vaccine.
- IXIARO does not protect against encephalitis caused by other viruses/pathogens.
- IXIARO does not protect against other diseases transmitted by mosquitoes.

What is Japanese encephalitis virus (JEV) and what is the disease caused by JEV?

Japanese encephalitis (JE) is caused by the Japanese encephalitis virus, JEV, which is mainly found in Asia. JEV is transmitted to humans by mosquitoes that have bitten an infected animal (like pigs). Many infected people develop mild symptoms or no symptoms at all. In people who develop severe disease, JE usually starts as a flu-like illness, with fever, chills, tiredness, headache, nausea, and vomiting. Confusion and agitation also occur in the early stage. JE causes death in one out of every three people with overt encephalitis. One out of two survivors develops permanent brain damage. JE acquired during pregnancy may cause intrauterine infection and miscarriage.

Who is at risk for Japanese encephalitis?

- People who live in, or travel to, areas where JEV circulates.
- Laboratory personnel who work with JEV.

Who should not get IXIARO?

You should not get IXIARO if you:

- are allergic to any of the ingredients in the vaccine. A list of ingredients can be found at the end of this leaflet.
- had an allergic reaction after getting a dose of the vaccine or any other JEV vaccine.

IXIARO is not approved for use in infants below the age of 2 months.

What should I tell my health care professional before I am vaccinated with IXIARO?

It is very important to tell your health care provider if you:

- have had an allergic reaction to a previous dose of IXIARO or any other JEV vaccine.
- have a bleeding disorder or a reduction in blood platelets, which increases risk of bleeding or bruising (thrombocytopenia) and cannot receive injections in the arm.
- have a weakened immune system, for example, due to a genetic defect or HIV infection.
- are or may be pregnant, or are breast feeding. IXIARO has not been studied in pregnant women or nursing mothers.
- currently have any illness with a fever of more than 100°F (37.8°C).
- take any medicines, even those you can buy over the counter.

How is IXIARO given?

IXIARO is given as an injection in the upper arm muscle in individuals 3 years of age and older. Infants 2 to 11 months of age are given the vaccine into the thigh. Children 12 to 35 months of age may be given the vaccine into the arm muscle (if the muscle is large enough) or into the thigh.

You will get a total of 2 doses of the vaccine. Ideally, the doses are given as:

- First dose: at a date you and your health care provider choose.
- Second dose: 28 days after the first dose.

Make sure that you get both doses. If you miss the second dose, your health care provider will decide when to give the missed dose. Be aware that protection is not reliable until 1 week after you receive the second dose of IXIARO.

Adults 18 years of age and older: if the second dose was administered more than 1 year ago, you should consult your health care provider on the need for a booster dose of IXIARO prior to potential re-exposure to JEV.

What are the possible side effects of IXIARO?

The most common side effects in adolescents >12 years of age and adults are headache, muscle pain and injection site reactions (e.g., pain, swelling, tenderness, redness). Nausea, skin rash, fatigue, flu-like illness, fever, irritability and loss of appetite may also occur.

The most common side effects in children below the age of 12 years are fever, irritability, diarrhea, vomiting, loss of appetite, injection site pain and injection site redness.

Contact your health care provider right away if you get any symptoms after receiving IXIARO that concern you.

Tell your health care provider if you have any of the following problems because these may be signs of an allergic reaction:

- difficulty breathing
- hoarseness or wheezing
- hives

- dizziness, weakness or fast heart beat

What are the ingredients of IXIARO?

Active Ingredient: purified components of inactivated Japanese encephalitis virus (JEV).

Inactive Ingredients: aluminum hydroxide and phosphate buffered saline (sodium chloride, potassium dihydrogen phosphate, disodium hydrogen phosphate).

Minute amounts of other substances remain in the vaccine as a result of the manufacturing process. Refer to the package insert for a complete list.

What else should I know about IXIARO?

This leaflet is a summary of information about IXIARO. If you would like more information, please talk to your health care professional.U.S.and international agencies (such as cdc.gov and who.int) also provide additional information about JEV and related travel advisories.

Issued September 2022

License Holder:

Valneva Austria GmbH, Vienna, Austria

Manufacturer:

Valneva Scotland Ltd., Livingston, UK

and

Distributed by:

Valneva USA, Inc.
Bethesda, MD 20814 USA

PACKAGE. LABEL PRINCIPAL DISPLAY PANEL-IXIARO

PACKAGE LABEL